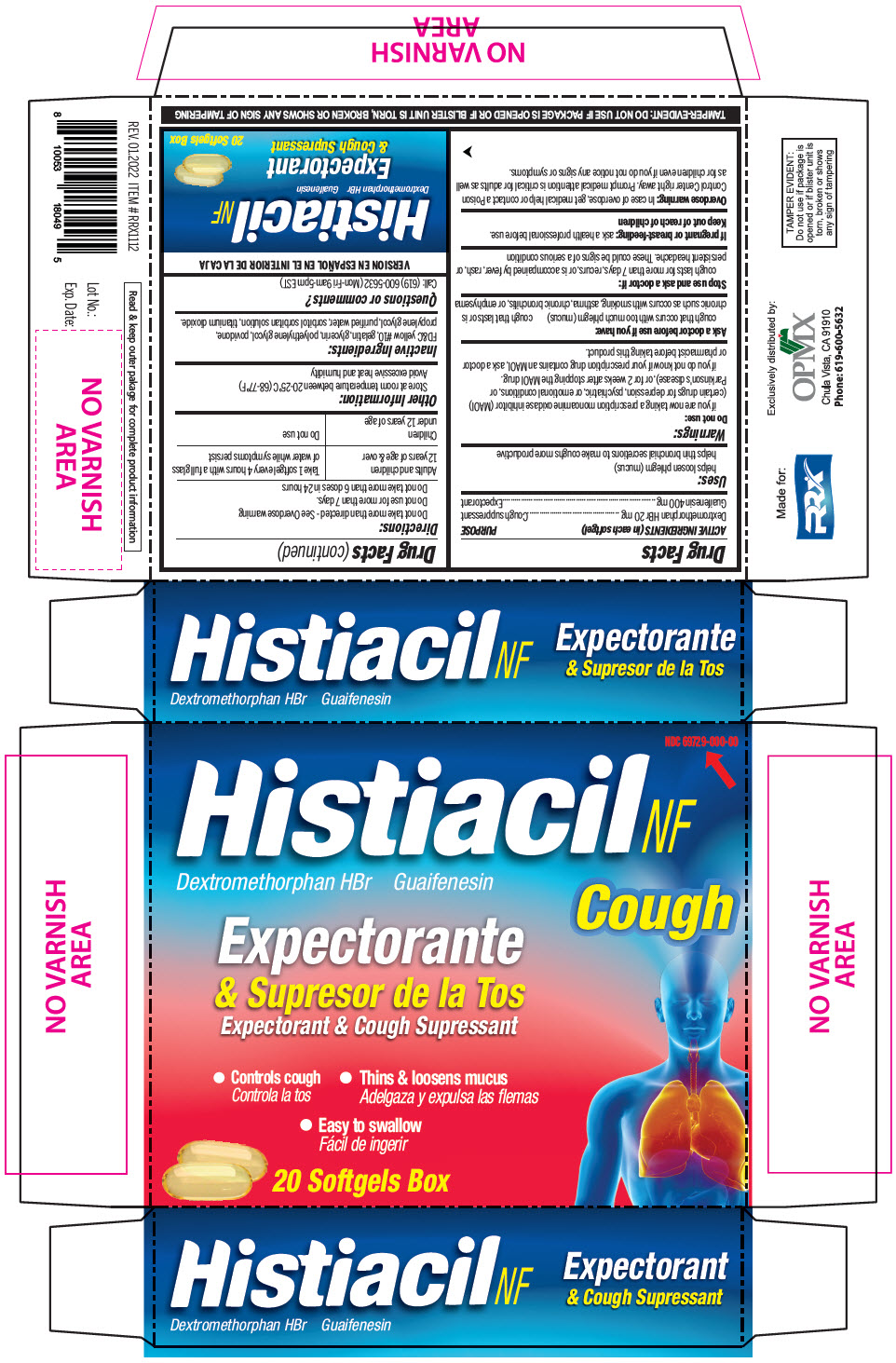 DRUG LABEL: Histiacil Cough
NDC: 69729-108 | Form: CAPSULE
Manufacturer: OPMX LLC
Category: otc | Type: HUMAN OTC DRUG LABEL
Date: 20240405

ACTIVE INGREDIENTS: DEXTROMETHORPHAN HYDROBROMIDE 20 mg/1 1; GUAIFENESIN 400 mg/1 1
INACTIVE INGREDIENTS: D&C YELLOW NO. 10; GELATIN, UNSPECIFIED; GLYCERIN; POLYETHYLENE GLYCOL, UNSPECIFIED; POVIDONE, UNSPECIFIED; PROPYLENE GLYCOL; WATER; TITANIUM DIOXIDE

Histiacil Cough

Drug Facts

ACTIVE INGREDIENT

ACTIVE INGREDIENTS (in each softgel) | PURPOSE
Dextromethorphan HBr 20 mg | Cough suppressant
Guaifenesin 400 mg | Expectorant

Uses

helps loosen phlegm (mucus)

helps thin bronchial secretions to make coughs more productive

Warnings

Do not use

if you are now taking a prescription monoamine oxidase inhibitor (MAOI) (certain drugs for depression, psychiatric, or emotional conditions, or Parkinson's disease), or for 2 weeks after stopping the MAOI drug.

if you do not know if your prescription drug contains an MAOI, ask a doctor or pharmacist before taking this product.

Ask a doctor before use if you have

cough that occurs with too much phlegm (mucus)

cough that lasts or is chronic such as occurs with smoking, asthma, chronic bronchitis, or emphysema

Stop use and ask a doctor if

cough lasts for more than 7 days, recurs, or is accompained by fever, rash, or persistent headache. These could be signs of a serious condition

PREGNANCY OR BREAST FEEDING

If pregnant or breast-feeding: ask a health professional before use.

Keep out of reach of children

Overdose warning

In case of overdose, get medical help or contact a Poison Control Center right away. Prompt medical attention is critical for adults as well as for children even if you do not notice any signs or symptoms.

Directions

Do not take more than directed - See Overdose warning

Do not use for more than 7 days.

Do not take more than 6 doses in 24 hours

Adults and children 12 years of age & over | Take 1 softgel every 4 hours with a full glass of water while symptoms persist
Children under 12 years of age | Do not use

Other Information

Store at room temperature between 20-25°C (68-77°F)

Avoid excessive heat and humidity

Inactive Ingredients

FD&C yellow #10, gelatin, glycerin, polyethylene glycol, povidone, propylene glycol, purified water, sorbitol sorbitan solution, titanium dioxide.

Questions or comments?

Call: (619) 600-5632 (Mon-Fri 9am-5pm EST)

Exclusively distributed by:
OPMX
Chula Vista, CA 91910

PRINCIPAL DISPLAY PANEL - 20 Softgel Blister Pack Box

NDC 69729-000-00

Histiacil NF

Dextromethorphan HBr
Guaifenesin

Cough

Expectorant & Cough Supressant

- Controls cough
- Thins & loosens mucus
- Easy to swallow

20 Softgels Box